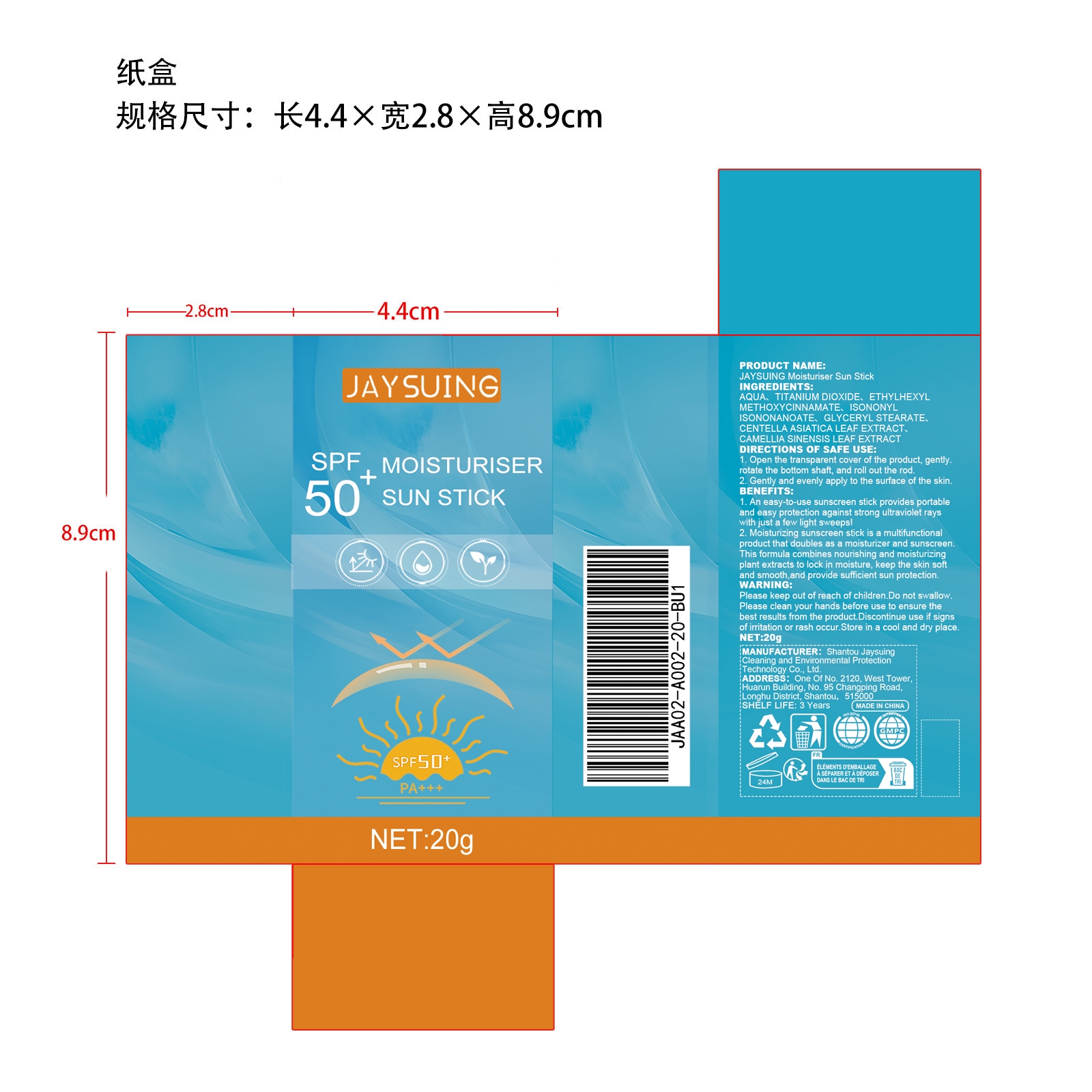 DRUG LABEL: JAYSUING Moisturiser Sun Stick
NDC: 85060-008 | Form: CREAM
Manufacturer: Shantou Jaysuing Cleaning and Environmental Protection Technology Co., Ltd.
Category: otc | Type: HUMAN OTC DRUG LABEL
Date: 20251127

ACTIVE INGREDIENTS: CENTELLA ASIATICA LEAF 0.06 mg/20 mg; CAMELLIA SINENSIS LEAF 0.004 mg/20 mg
INACTIVE INGREDIENTS: ETHYLHEXYL METHOXYCINNAMATE 1 mg/20 mg; ISONONYL ISONONANOATE 0.8 mg/20 mg; GLYCERYL STEARATE 0.3 mg/20 mg; AQUA 16.236 mg/20 mg; TITANIUM DIOXIDE 1.6 mg/20 mg

Active Ingredient(s)

CENTELLA ASIATICA LEAF EXTRACT、CAMELLIA SINENSIS LEAF EXTRACT

Purpose

1. An easy-to-use sunscreen stick provides portable and easy protection against strong ultraviolet rays with just a few light sweeps!

2. Moisturizing sunscreen stick is a multifunctional product that doubles as a moisturizer and sunscreen. This formula combines nourishing and moisturizing plant extracts to lock in moisture, keep the skin soft and smooth,and provide sufficient sun protection.

Using

1. Open the transparent cover of the product, gently. Rotate the bottom shaft, and roll out the rod.

2. Gently and evenly apply to the surface of the skin.

Warning

Please keep out of reach of children. Do not swallow.Please clean your hands before use to ensure the best results from the product. Discontinue use if signs of irritation or rash occur. Store in a cool and dry place.

Do Not Use

Discontinue use if signs of irritation or rash occur.

Stop Use

Discontinue use if signs of irritation or rash occur.

KEEP OUT OF REACH OF CHILDREN

Please keep out of reach of children. Do not swallow.

STORAGE AND HANDLING

Store in a cool and dry place.

INACTIVE INGREDIENT

AQUA、TITANIUM DIOXIDE、ETHYLHEXYL METHOXYCINNAMATE、ISONONYL ISONONANOATE、 GLYCERYL STEARATE

INDICATIONS AND USAGE

1. Open the transparent cover of the product, gently. Rotate the bottom shaft, and roll out the rod.

2. Gently and evenly apply to the surface of the skin.

DOSAGE AND ADMINISTRATION

1. Open the transparent cover of the product, gently. Rotate the bottom shaft, and roll out the rod.

2. Gently and evenly apply to the surface of the skin.